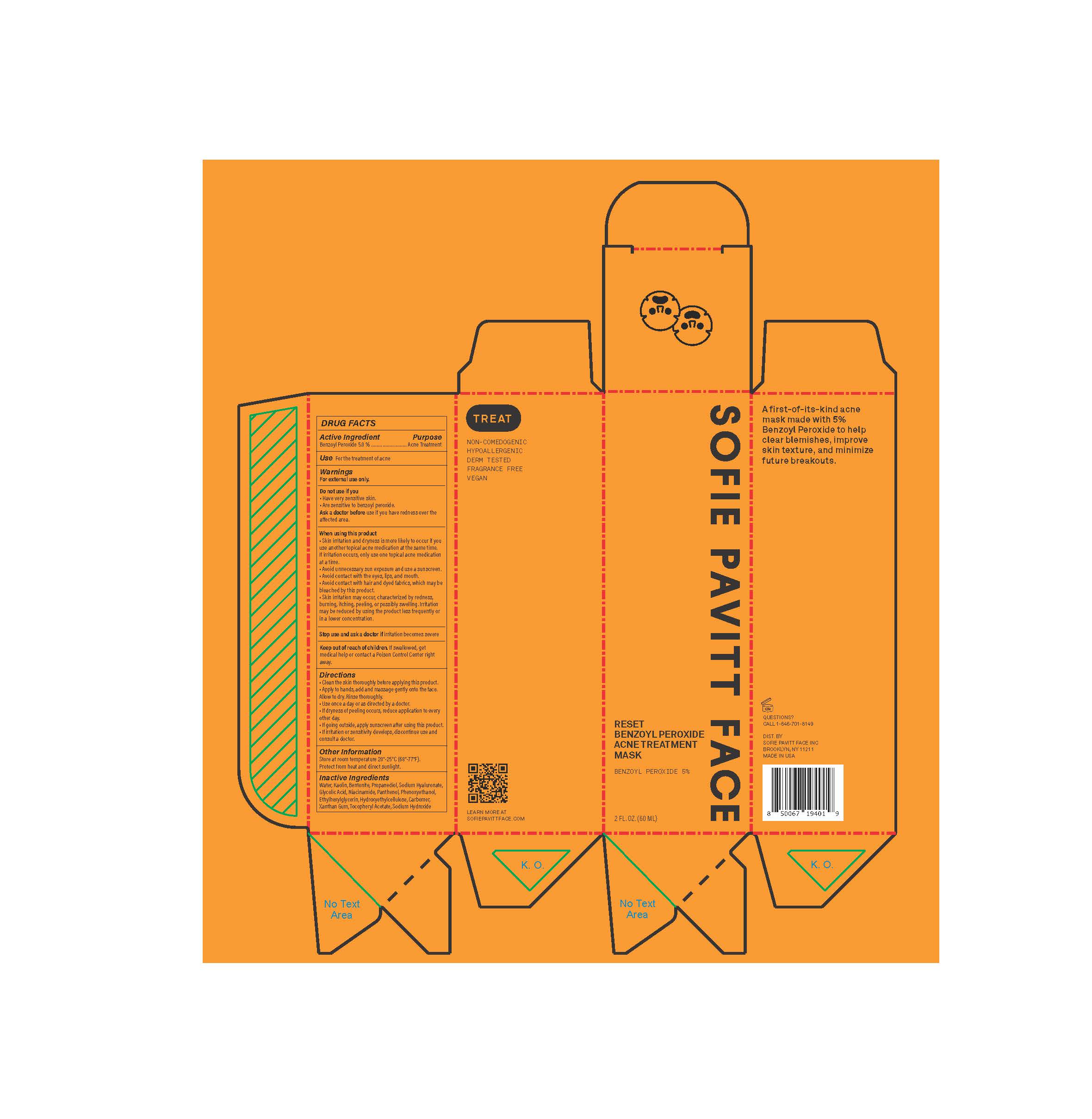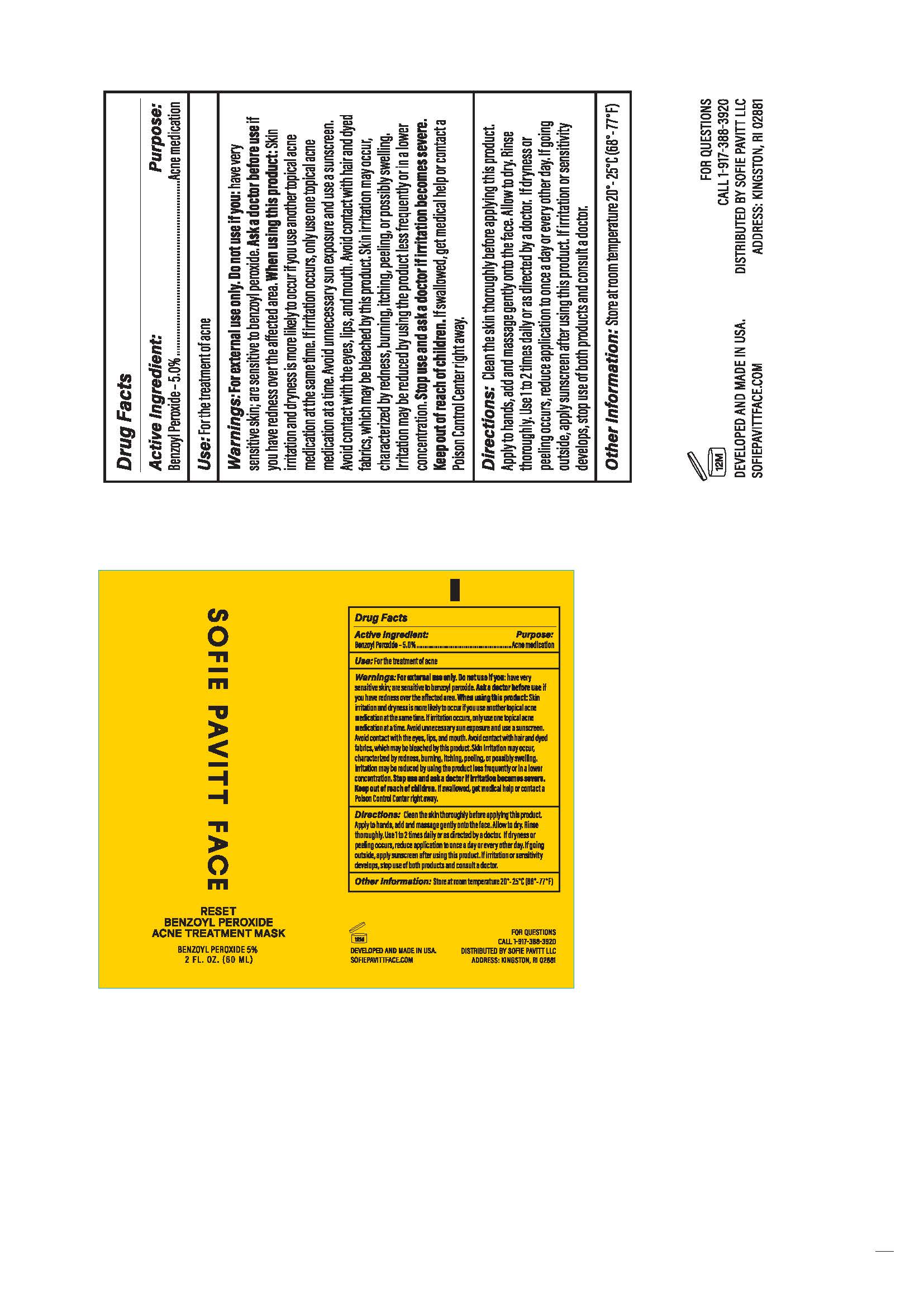 DRUG LABEL: Sofie Pavitt Face Reset Benzoyl Peroxide Acne Treatment Mask
NDC: 52261-7301 | Form: PASTE
Manufacturer: Cosco International, Inc.
Category: otc | Type: HUMAN OTC DRUG LABEL
Date: 20241111

ACTIVE INGREDIENTS: Benzoyl Peroxide 0.05 kg/1 kg
INACTIVE INGREDIENTS: WATER; KAOLIN; BENTONITE; PROPANEDIOL; HYALURONATE SODIUM; PHENOXYETHANOL; ETHYLHEXYLGLYCERIN; GLYCOLIC ACID; NIACINAMIDE; PANTHENOL; HYDROXYETHYL CELLULOSE, UNSPECIFIED; XANTHAN GUM; CARBOMER; .ALPHA.-TOCOPHEROL ACETATE; SODIUM HYDROXIDE

Sofie Pavitt Face Reset Benzoyl Peroxide Acne Treatment Mask

Active Ingredient/Purpose

Benzoyl Peroxide............Acne Treatment

Use

For the treatment of acne

Warnings

For external use only

Do not use if you

- have very sensitive skin
- are sensitive to benzoyl peroxide

Ask doctor before use

if you have redness over the affected area

When using this product

- Skin irritation and dryness is more likely to occur if you use another topical acne medication at the same time. If irritation occurs, only use one topical acne medication at a time.
- Avoid unnecessary sun exposure and use a sunscreen
- Avoid contact with the eyes, lips, and mouth
- Avoid contact with hair and dyed fabrics, which may be bleached by this product
- Skin irritation may occur, characterized by redness, burning, itching, peeling, or possibly swelling. Irritation may be reduced by using the product less frequently or in a lower concentration.

Stop use and ask a doctor if

irritation becomes severe

Keep out of reach of children.

If swallowed, get medical help, or contact a Poison Control Center right away.

Directions

- Clean the skin throughly before applying this product
- Apply to hands, add and massage gently onto the face. Allow to dry. Rinse thoroughly.
- Use once a day or as directed by a doctor.
- If dryness or peeling occurs, reduce application to once every other day.
- If going outside, apply sunscreen after using this product.
- If irritation or sensitivity develops, discontinue use and consult a doctor.

Other Information

Store at room temperature 20°-25°C (68°-77°F)

Protect from heat and direct sunlight.

Inactive Ingredients

Water, Kaolin, Bentonite, Propanediol, Sodium Hyaluronate, Glycolic Acid, Niacinamide, Panthenol, Phenoxyethanol, Ethylhexylglycerin, Hydroxyethylcellulose, Carbomer, Xanthan Gum, Tocopheryl Acetate, Sodium Hydroxide